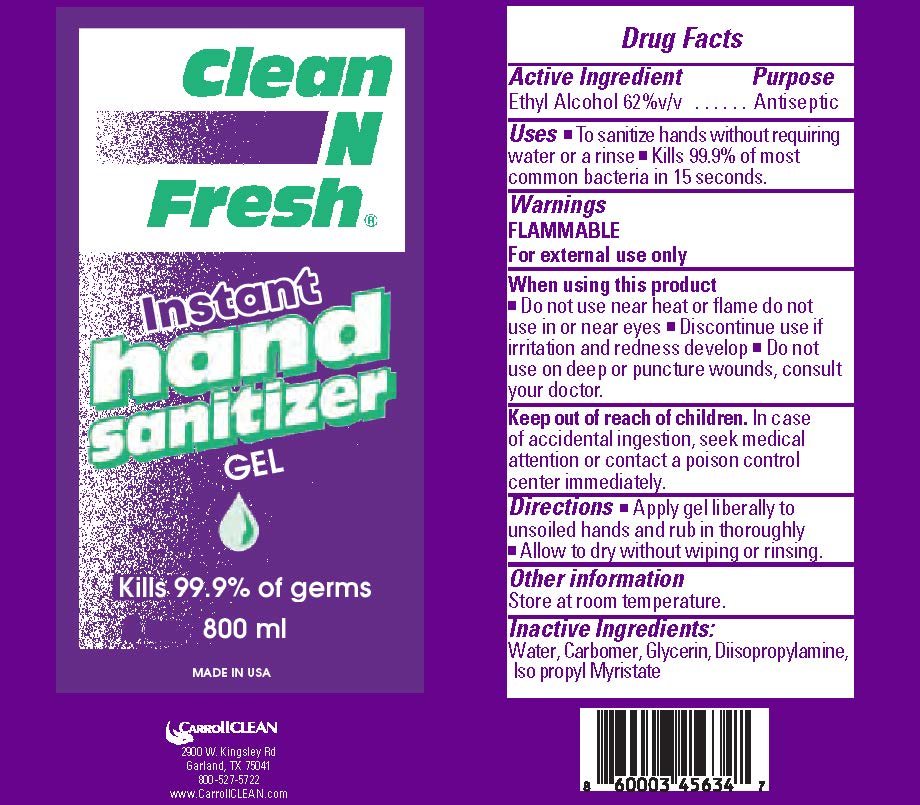 DRUG LABEL: Clean N Fresh Instant Hand Sanitizer Antibacterial
NDC: 73708-514 | Form: GEL
Manufacturer: CarrollCLEAN LLC
Category: otc | Type: HUMAN OTC DRUG LABEL
Date: 20201102

ACTIVE INGREDIENTS: ALCOHOL 147 mL/236 mL
INACTIVE INGREDIENTS: CARBOMER INTERPOLYMER TYPE A (55000 CPS) 0.75 mL/236 mL; DIISOPROPYLAMINE 0.39 mL/236 mL; WATER 87.17 mL/236 mL; GLYCERIN 0.45 mL/236 mL; ISOPROPYL MYRISTATE 0.23 mL/236 mL

Clean N Fresh (r) Hand Sanitizer

Active Ingredient

Ethyl Alcohol 62% v/v

Purpose

Antiseptic

Uses

*To sanitize hands without requiring water or a rinse*Kills 99.9% of most common bacteria in 15 seconds.

Warnings

FLAMMABLE

For external use only

When using this product

*Do not use near heat or flame do not use in or near eyes * Discontinue use if irritation and redness develop * Do not use on deep or puncture wounds, consult your doctor.

Keep out of reach of children.

In case of accidental ingestion, seek medical attention or contact a poison control center immediately.

Directions

*Apply gel liberally to unsoiled hands and rub in thoroughly * Allow to dry without wiping or rinsing.

Other information

Store at room temperature.

Inactive Ingredients:

Water, Carbomer, Glycerin, Diisopropylamine, Iso propyl Myristate